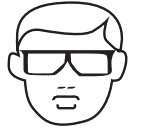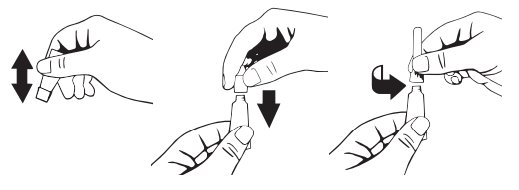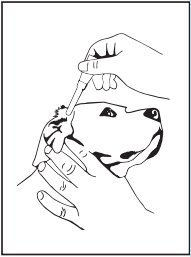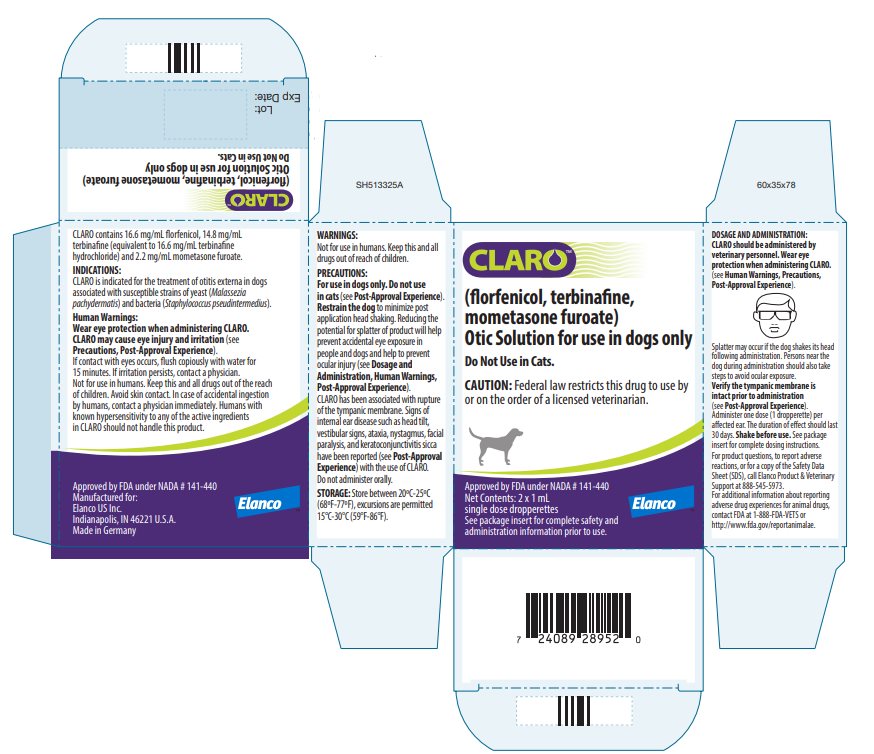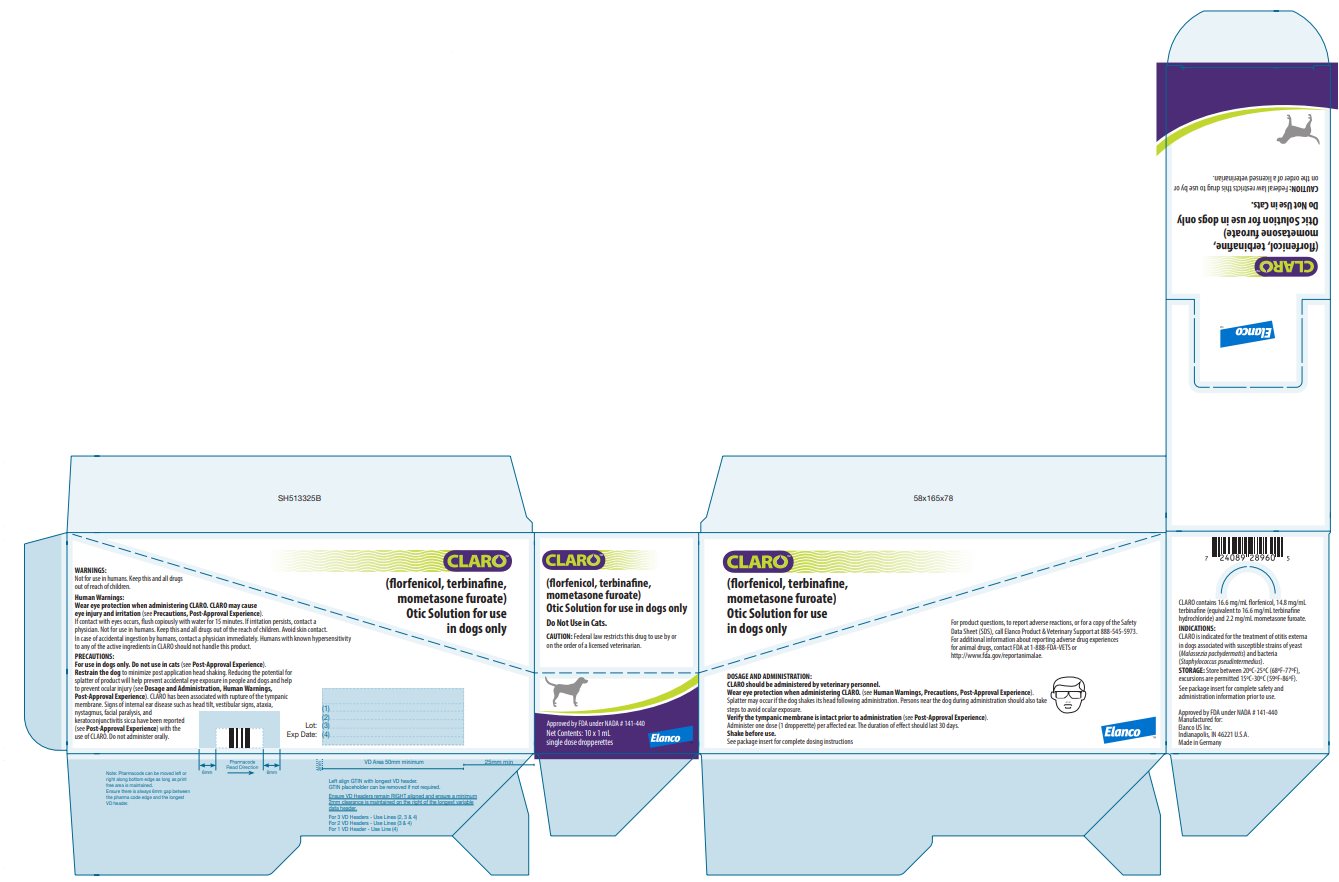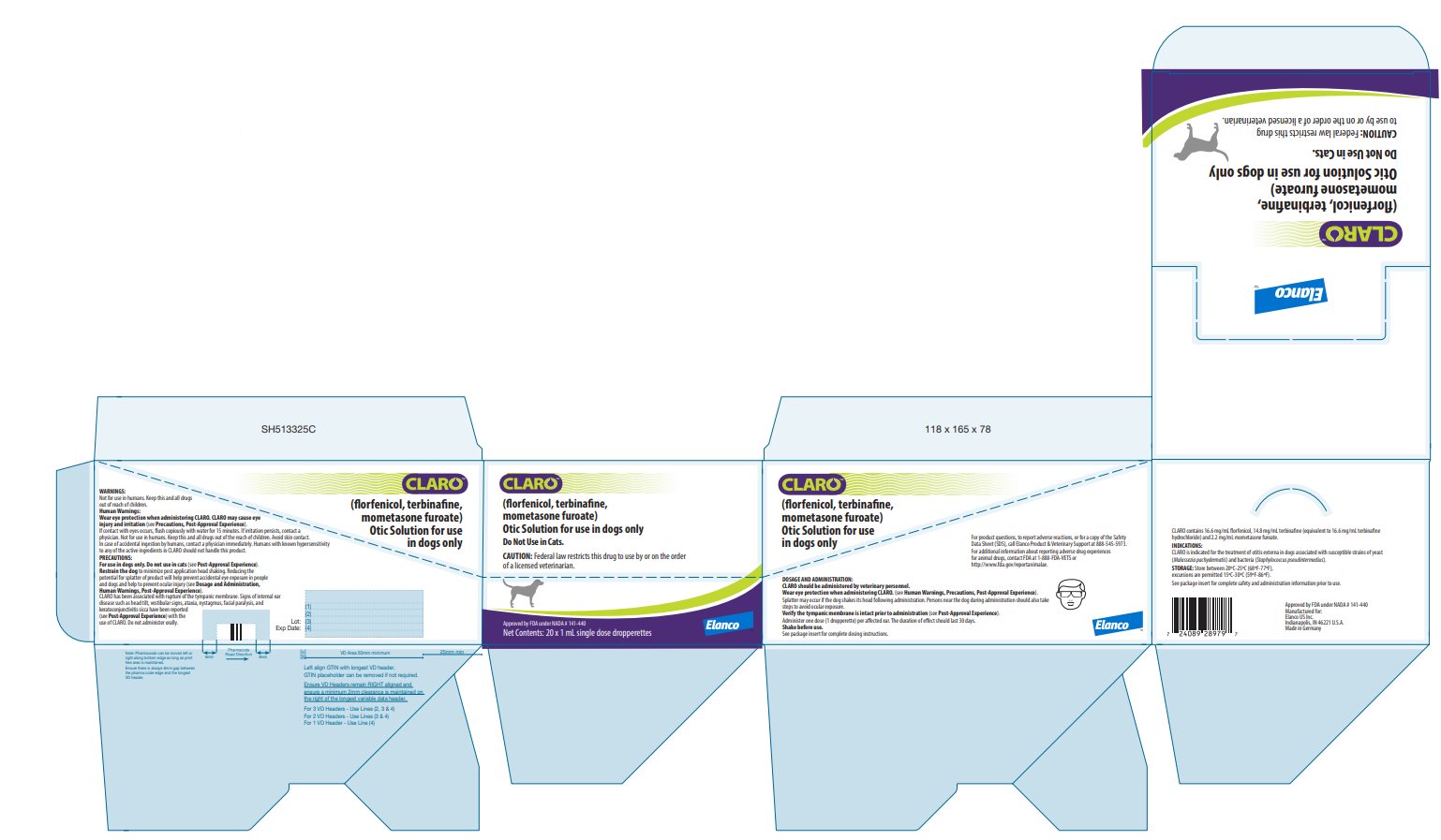 DRUG LABEL: Claro
NDC: 58198-0027 | Form: SOLUTION
Manufacturer: Elanco US Inc.
Category: animal | Type: PRESCRIPTION ANIMAL DRUG LABEL
Date: 20250722

ACTIVE INGREDIENTS: FLORFENICOL 16.6 mg/1 mL; TERBINAFINE 14.8 mg/1 mL; MOMETASONE FUROATE 2.2 mg/1 mL

CLARO™
ElancoTM
(florfenicol, terbinafine, mometasone furoate)

Otic Solution for use in dogs only

Do Not Use in Cats.

Antibacterial, antifungal, and anti-inflammatory

CAUTION: Federal law restricts this drug to use by or on the order of a licensed veterinarian.

DESCRIPTION:

CLARO contains 16.6 mg/mL florfenicol, 14.8 mg/mL terbinafine (equivalent to 16.6 mg/mL terbinafine hydrochloride) and 2.2 mg/mL mometasone furoate. Inactive ingredients include purified water, propylene carbonate, propylene glycol, ethyl alcohol, and polyethylene glycol.

INDICATIONS:

CLARO is indicated for the treatment of otitis externa in dogs associated with susceptible strains of yeast (Malassezia pachydermatis) and bacteria (Staphylococcus pseudintermedius).

DOSAGE AND ADMINISTRATION:

CLARO should be administered by veterinary personnel.

Wear eye protection when administering CLARO. (see Human Warnings, Precautions, Post-Approval Experience).

Splatter may occur if the dog shakes its head following administration. Persons near the dog during administration should also take steps to avoid ocular exposure.

Shake before use.

Verify the tympanic membrane is intact prior to administration. (see Contraindications, Precautions, Post-Approval Experience).

Administer one dose (1 dropperette) per affected ear.

1. Clean and dry the external ear canal before administering the product.
2. Verify the tympanic membrane is intact prior to administration.
3. Remove single dose dropperette from the package.
4. While holding the dropperette in an upright position, remove the cap from the dropperette.
5. Turn the cap over and push the other end of the cap onto the tip of the dropperette.
6. Twist the cap to break the seal and then remove cap from the dropperette.
7. Screw the applicator nozzle onto the dropperette.
8. Insert the tapered tip of the dropperette into the affected external ear canal and squeeze to instill the entire contents (1 mL) into the affected ear.
9. Gently massage the base of the ear to allow distribution of the solution.
  Restrain the dog to minimize post application head shaking to reduce potential for splatter of product and accidental eye exposure in people and dogs (see Post-Approval Experience).

10. Repeat with other ear as prescribed.
11. The duration of the effect should last 30 days. Cleaning the ear after dosing may affect product effectiveness.

CONTRAINDICATIONS:

Do not use in dogs with known tympanic membrane perforation (see Precautions).

CLARO is contraindicated in dogs with known or suspected hypersensitivity to florfenicol, terbinafine hydrochloride, or mometasone furoate.

WARNINGS:

Human Warnings: CLARO may cause eye injury and irritation (see Precautions, Post-Approval Experience).

If contact with eyes occurs, flush copiously with water for at least 15 minutes. If irritation persists, contact a physician.

Humans with known hypersensitivity to any of the active ingredients in CLARO should not handle this product.

Not for use in humans. Keep this and all drugs out of the reach of children. Avoid skin contact. In case of accidental ingestion by humans, contact a physician immediately.

PRECAUTIONS:

For use in dogs only. Do not use in cats (see Post-Approval Experience).

Wear eye protection when administering CLARO and restrain the dog to minimize post application head shaking. Reducing the potential for splatter of product will help prevent accidental eye exposure in people and dogs and help to prevent ocular injury (see Dosage and Administration, Human Warnings, Post-Approval Experience).

Proper patient selection is important when considering the benefits and risks of using CLARO. The integrity of the tympanic membrane should be confirmed before administering the product.

CLARO has been associated with rupture of the tympanic membrane. Reevaluate the dog if hearing loss or signs of vestibular dysfunction are observed during treatment.

Signs of internal ear disease such as head tilt, vestibular signs, ataxia, nystagmus, facial paralysis, and keratoconjunctivitis sicca have been reported (see Post-Approval Experience) with the use of CLARO.

Do not administer orally.

Use of topical otic corticosteroids has been associated with adrenocortical suppression and iatrogenic hyperadrenocorticism in dogs (see Animal Safety).

Use with caution in dogs with impaired hepatic function (see Animal Safety).

The safe use of CLARO in dogs used for breeding purposes, during pregnancy, or in lactating bitches, has not been evaluated.

ADVERSE REACTIONS:

In a field study conducted in the United States (see Effectiveness), there were no directly attributable adverse reactions in 146 dogs administered CLARO.

POST-APPROVAL EXPERIENCE (2019):

The following adverse events are based on post-approval adverse drug experience reporting for CLARO. Not all adverse events are reported to FDA/CVM. It is not always possible to reliably estimate the adverse event frequency or establish a causal relationship to product exposure using these data.

In humans, accidental exposure leading to corneal ulcers and other ocular injuries such as eye irritation and redness have been reported. Exposure occurred when the dog shook its head after application of CLARO. Skin irritation has also been reported.

In dogs, the adverse events reported are presented below in decreasing order of reporting frequency:
Ear discharge, head shaking, ataxia, internal ear disorder (head tilt and vestibular), deafness, emesis, nystagmus, pinnal irritation and ear pain, keratoconjunctivitis sicca, vocalization, corneal ulcer, cranial nerve disorder (facial paralysis), tympanic membrane rupture.

CLARO is not approved for use in cats. The adverse events reported following extra-label use in cats are presented below in decreasing order of reporting frequency:
Ataxia, anorexia, internal ear disorder (head tilt and vestibular), Horner’s syndrome (third eyelid prolapse and miosis), nystagmus, lethargy, anisocoria, head shake, emesis, tympanic rupture, and deafness.

CONTACT INFORMATION:

For product questions, to report adverse reactions, or for a copy of the Safety Data Sheet (SDS), call Elanco Product & Veterinary Support at 888-545-5973.

For additional information about reporting adverse drug experi- ences for animal drugs, contact FDA at 1-888-FDA-VETS or http://www.fda.gov/reportanimalae.

Information for Dog Owners:

Owners should be aware that adverse reactions may occur following administration of CLARO and should be instructed to observe the dog for signs such as ear pain and irritation, vomiting, head shaking, head tilt, incoordination, eye pain and ocular discharge (see Post-Approval Experience). Owners should be advised to contact their veterinarian if any of the above signs are observed.

Owners should also be informed that splatter may occur if the dog shakes its head following administration of CLARO which may lead to ocular exposure. Eye injuries, including corneal ulcers, have been reported in humans and dogs associated with head shaking and splatter following administration. Owners should be careful to avoid ocular exposure (see Precautions, Post-Approval Experience).

PHARMACOLOGY:

CLARO Otic Solution is a fixed combination of three active substances: florfenicol (antibacterial), terbinafine (antifungal), and mometasone furoate (steroidal anti-inflammatory). Florfenicol is a bacteriostatic antibiotic which acts by inhibiting protein synthesis. Terbinafine is an antifungal which selectively inhibits the early synthesis of ergosterol. Mometasone furoate is a glucocorticosteroid with anti-inflammatory activity.

MICROBIOLOGY:

The compatibility and additive effect of each of the components in CLARO solution was demonstrated in a component effectiveness and non-interference study. An in vitro study of organisms collected from clinical cases of otitis externa in dogs enrolled in the clinical effectiveness study determined that florfenicol and terbinafine hydrochloride inhibit the growth of bacteria and yeast commonly associated with otitis externa in dogs. No consistent synergistic or antagonistic effect of the two antimicrobials was demonstrated. The addition of mometasone furoate to the combination did not impair antimicrobial activity to any clinically significant extent. In a field study (see Effectiveness), at least 10 isolates from successfully treated cases were obtained for S. pseudintermedius and M. pachydermatis.

EFFECTIVENESS:

In a well-controlled, double-masked field study, CLARO was evaluated against a vehicle control in 221 dogs with otitis externa. One hundred and forty six dogs were treated with CLARO and 75 dogs were treated with the vehicle control. All dogs were evaluated for safety. Treatment (1 mL) was administered once on Day 0 to the affected ear(s). Prior to treatment, the ear(s) was cleaned with saline. The dogs were evaluated on Days 0, 7, 14, and 30. Blood work and urinalysis were obtained on Day 0 pre-treatment and Day 30 at study completion. Four clinical signs associated with otitis externa were evaluated: erythema, exudate, swelling, and ulceration. Success was based on clinical improvement at Day 30. Of the 183 dogs included in the effectiveness evaluation, 72.5% of dogs administered CLARO solution were successfully treated, compared to 11.1% of the dogs in the vehicle-control group (p = 0.0001).

ANIMAL SAFETY:

In a target animal safety study, CLARO was administered aurally to 12-week-old Beagle puppies (4 dogs/sex/group) at 0X, 1X, 3X, and 5X the recommended dose once every 2 weeks for a total dosing period of 28 days (3 times the treatment duration). No clinically relevant treatment-related findings were noted in hearing tests, body weight, weight gain, or food consumption. CLARO administration was associated with post-treatment ear wetness or clear aural exudate, increased absolute neutrophil count, decreased absolute lymphocyte and eosinophil counts, suppression of the adrenal cortical response to ACTH-stimulation, decreased adrenal weight and atrophy of the adrenal cortex, increased liver weight with hepatocellular enlargement/cytoplasmic change, and decreased thymus weight. Other potentially treatment-related effects included mild changes to AST, total protein, inorganic phosphorus, creatinine, and calcium.

STORAGE INFORMATION:

Store between 20°C – 25°C (68°F – 77°F), excursions are permitted 15°C – 30°C (59°F – 86°F).

HOW SUPPLIED:

CLARO solution is supplied in a single-use dropperette in a blister.
Each dropperette contains one 1 mL dose.
CLARO is available in cartons of two, ten, or twenty dropperettes.

Manufactured for:
Elanco US Inc.
Indianapolis, IN 46221 U.S.A.
Made in Germany
CLARO, Elanco and the diagonal bar logo are trademarks of Elanco or its affiliates.
© 2025 Elanco or its affiliates.

Approved by FDA under NADA # 141-440

Revised: May 2025
PA513325X

ElancoTM

Principal Display Panel - 1 mL Carton Label

CLARO™
(florfenicol, terbinafine,
mometasone furoate)

Otic Solution for use in dogs only

Do Not Use in Cats.

CAUTION: Federal law restricts this drug to use by
or on the order of a licensed veterinarian.

Approved by FDA under NADA # 141-440

Net Contents: 2 x 1 mL
single dose dropperettes

See package insert for complete safety and
administration information prior to use.

Elanco™

CLARO™
(florfenicol, terbinafine,
mometasone furoate)

Otic Solution for use in dogs only

Do Not Use in Cats.

CAUTION: Federal law restricts this drug to use by or
on the order of a licensed veterinarian.

Approved by FDA under NADA # 141-440

Net Contents: 10 x 1 mL
single dose dropperettes

Elanco™

CLARO™
(florfenicol, terbinafine,
mometasone furoate)

Otic Solution for use in dogs only

Do Not Use in Cats.

CAUTION: Federal law restricts this drug to use by or on the order
of a licensed veterinarian.

Approved by FDA under NADA # 141-440

Net Contents: 20 x 1 mL single dose dropperettes

Elanco™